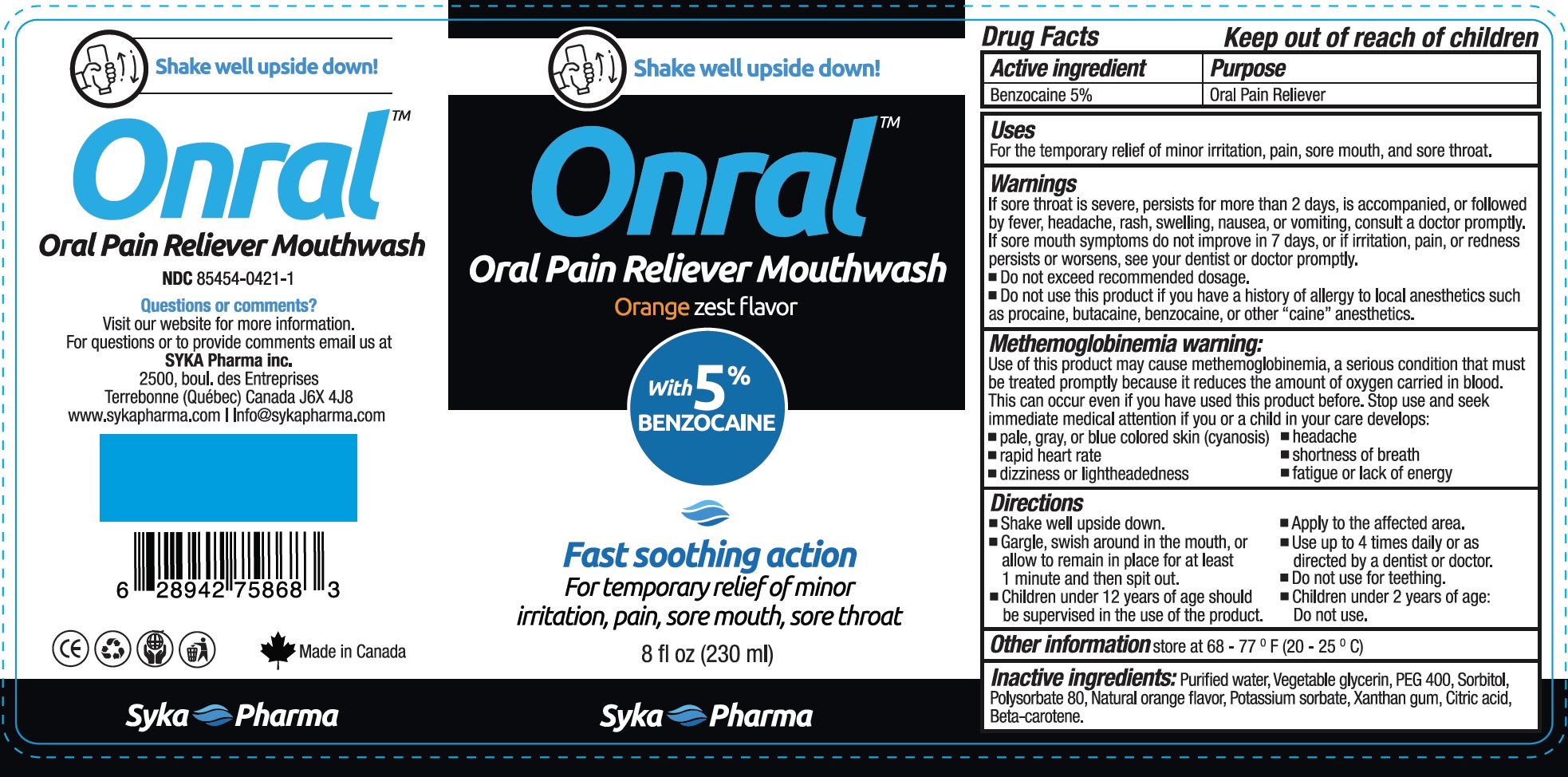 DRUG LABEL: Onral Oral Pain Reliever Mouthwash
NDC: 85454-0421 | Form: LIQUID
Manufacturer: Syka Pharma Inc.
Category: otc | Type: HUMAN OTC DRUG LABEL
Date: 20250603

ACTIVE INGREDIENTS: BENZOCAINE 50 mg/1 mL
INACTIVE INGREDIENTS: WATER; POLYETHYLENE GLYCOL 400; SORBITOL; POLYSORBATE 80; POTASSIUM SORBATE; XANTHAN GUM; CITRIC ACID MONOHYDRATE; BETA CAROTENE

Onral Oral Pain Reliever Mouthwash

Active ingredient

Benzocaine 5%

Purpose

Oral Pain Reliever

Uses

For the temporary relief of minor irritation, pain, sore mouth, and sore throat.

Warnings

If sore throat is severe, persists for more than 2 days, is accompanied, or followed by fever, headache, rash, swelling, nausea, or vomiting, consult a doctor promptly. If sore mouth symptoms do not improve in 7 days, or if irritation, pain, or redness persists or worsens, see your dentists or doctor promptly.

- Do not exceed recommended dosage.

Do not use

- this product if you have a history of allergy to local anesthetics such as procaine, butacaine, or other "caine" anesthetics.

Methemoglobinemia warning:

Use of this product may cause methemoglobinemia, a serious condition that must be treated promptly because it reduce the amount of oxygen carried in blood. This can occur even if you have used this product before.

Stop use and seek immediate medical attention

if you or a child in your care develops:

- pale, gray, or blue colored skin (cyanosis)
- rapid heart rate
- dizziness or lightheadedness
- headache
- shortness of breath
- atigue or lack of energy

Directions

- Shake well upside down.
- Gargle, swish around in the mouth, or allow to remain in place for at least 1 minute and then spit out.
- Children under 12 years of age should be supervised in the use of the product.
- Apply to the affected area.
- Use up to 4 times daily or as directed by a dentist or doctor.
- Do not use for teething.
- Children under 2 years of age: Do not use.

Other information

store at 68-77 ° F (20-25 ° C)

Inactive ingredients:

Purified water, Vegetable glycerin, PEG 400, Sorbitol, Polysorbate 80, Natural orange flavor, Potassium sorbate, Xanthan gum, Citric acid, Beta-carotene.